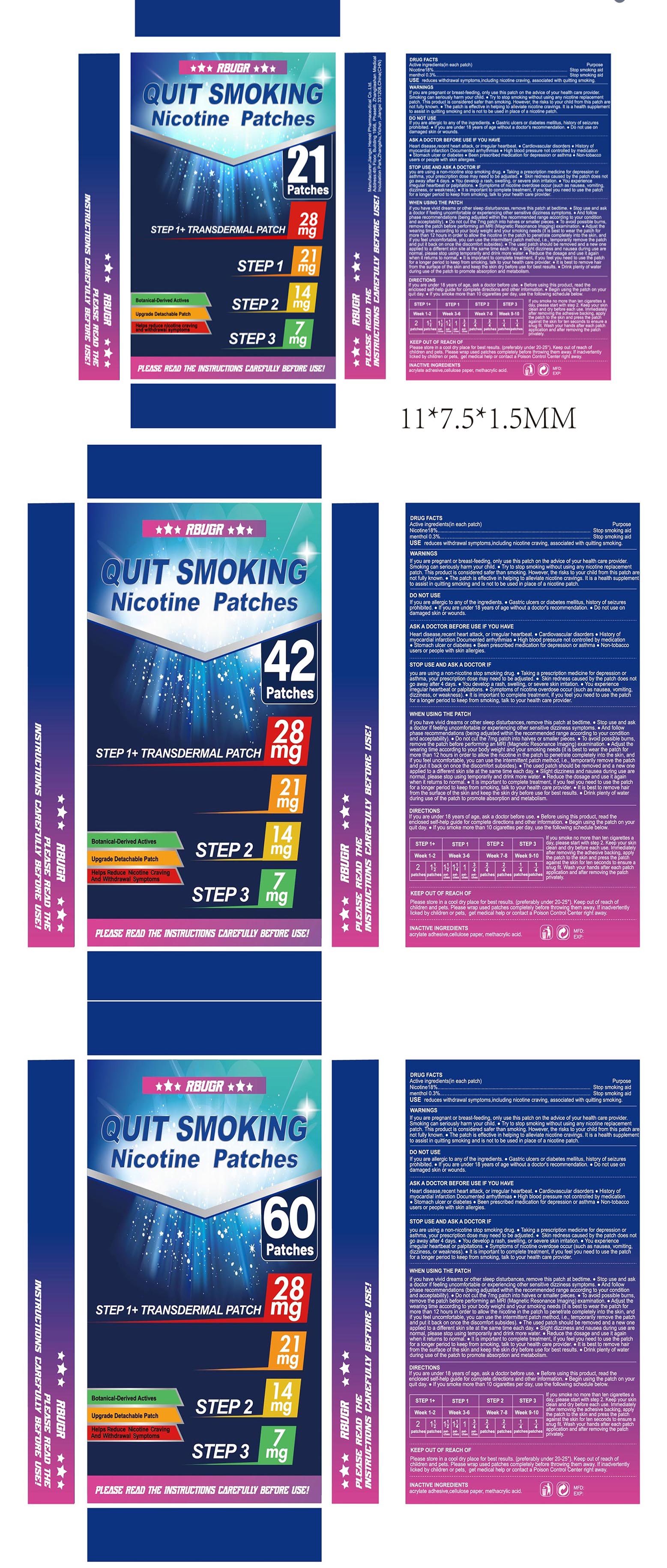 DRUG LABEL: RBUGR QUIT SMOKING Nicotine Patches
NDC: 87165-001 | Form: PATCH
Manufacturer: Nanjing Ludejin Corporation Management Co., Ltd
Category: otc | Type: HUMAN OTC DRUG LABEL
Date: 20251015

ACTIVE INGREDIENTS: MENTHOL 0.003 g/1 1; NICOTINE 0.18 g/1 1
INACTIVE INGREDIENTS: METHACRYLIC ACID

87165-001 RBUGR QUIT SMOKING Nicotine Patches

ACTIVE INGREDIENT

Nicotine18%
menthol 0.3%

PURPOSE

Stop smoking aid

INDICATIONS AND USAGE

USE reduces withdrawal symptoms,including nicotine craving, associated with quitting smoking.

WARNINGS

If you are pregnant or breast-feeding, only use this patch on the advice of your health care provider.Smokina can seriously harm vour child. Try to stop smoking without using any nicotine replacement patch. This product is considered safer than smoking. However, the risks to your child from this patch are not fully known. The patch is effective in helping to alleviate nicotine cravings. lt is a health supplement to assist in quitting smoking and is not to be used in place of a nicotine patch.

DO NOT USE

If you are allergic to any of the ingredients. e Gastric ulcers or diabetes mellitus, history of seizures prohibited. lf you are under 18 years of age without a doctor's recommendation. Do not use on damaged skin or wounds.

ASK A DOCTOR BEFORE USE IF YOU HAVE
Heart disease,recent heart attack, or irregular heartbeat. , Cardiovascular disorders History ofmyocardial infarction Documented arrhythmias High blood pressure not controlled by medication Stomach ulcer or diabetes Been prescribed medication for depression or asthma Non-tobaccousers or people with skin allergies.

WHEN USING THE PATCH
if you have vivid dreams or other sleep disturbances, remove this patch at bedtime. e Stop use and aska doctor if feeling uncomfortable or experiencing other sensitive dizziness symptoms. o And followphase recommendations (being adjusted within the recommended range according to your conditionand acceptability). o Do not cut the 7mg patch into halves or smaller pieces. To avoid possible burns.remove the patch before performing an MRl (Magnetic Resonance lmaging) examination. Adjust thewearing time according to your body weight and your smoking needs it is best to wear the patch formore than 12 hours in order to allow the nicotine in the patch to penetrate completely into the skin, andif you feel uncomfortable, you can use the intermittent patch method, i.e., temporarily remove the patchand put it back on once the discomfort subsides). e The used patch should be removed and a new oneapplied to a different skin site at the same time each day. Slight dizziness and nausea during use arenormal, please stop using temporarily and drink more water. Reduce the dosage and use it aaainwhen it returns to norma. it is important to complete treatment, if you feel you need to use the patchfor a longer period to keep from smoking, talk to your health care provider. lt is best to remove hairfrom the surface of the skin and keep the skin dry before use for best results. o Drink plenty of waterduring use of the patch to promote absorption and metabolism.

STOP USE

you are using a non-nicotine stop smoking drug. Taking a prescription medicine for depression orasthma, your prescription dose may need to be adiusted. o Skin redness caused by the patch does notgo away after 4 days. You develop a rash, swelling, or severe skin irritation. You experienceirreqular heartbeat or palpitations.o Symptoms of nicotine overdose occur (such as nausea, vomitingdizziness, or weakness). lt is important to complete treatment, if you feel you need to use the patchfor a longer period to keep from smoking, talk to your health care provider.

KEEP OUT OF REACH OF CHILDREN

Please store in a cool dry place for best results. (preferably under 20-25°). Keep out of reach ofchildren and pets, Please wrap used patches completely before throwing them away. lf inadvertentlylicked by children or pets, get medical help or contact a Poison Control Center right away.

DIRECTIONS
If you are under 18 years of age, ask a doctor before use. e Before using this product, read the enclosed self-help guide for complete directions and other information. Begin using the patch on your quit day. o lf you smoke more than 10 cigarettes per day, use the following schedule below.
lf you smoke no more than ten cigarettes aday, please start with step 2. Keep your skinclean and dry before each use. lmmediatelyafter removing the adhesive backing, applythe patch to the skin and press the patchagainst the skin for ten seconds to ensure asnug fit. Wash your hands after each patchapplication and after removing the patchprivately.

INACTIVE INGREDIENT

acrylate adhesive,cellulose paper, methacrylic acid